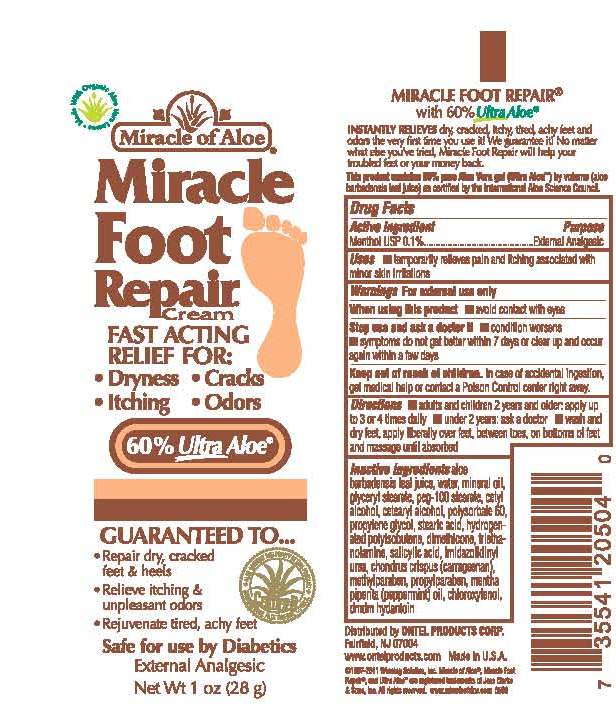 DRUG LABEL: Miracle Foot Repair 
NDC: 66391-0504 | Form: CREAM
Manufacturer: Winning Solutions
Category: otc | Type: HUMAN OTC DRUG LABEL
Date: 20110901

ACTIVE INGREDIENTS: MENTHOL  0.028 g/28 g
INACTIVE INGREDIENTS: ALOE VERA LEAF ; Water; MINERAL OIL; Stearic Acid; PEG-100 STEARATE; GLYCERYL MONOSTEARATE; CETOSTEARYL ALCOHOL; POLYSORBATE 60; PROPYLENE GLYCOL; Cetyl Alcohol; COCOA BUTTER; TROLAMINE; SALICYLIC ACID; CHONDRUS; CHAMOMILE; Methylparaben; Propylparaben; DMDM HYDANTOIN

Active Ingredient : MENTHOL 0.1%

Purpose : External Analgesic

Warnings: For external use only .

Keep out of reach of children : In case of accidental ingestion, get medical help or contact a Poison Control center right away.

DOSAGE AND ADMINISTRATION

Directions : adults and children 2 years and older apply as needed

under 2 years ask a doctor.

wash and dry skin apply liberatly over attached area and massage until absorbed .

INDICATIONS AND USAGE

Uses: Temporary protects and helps relieve chapped or cracked skin

INACTIVE INGREDIENT

aloe barabardensis leaf Juice , water , mineral oil , glyceryl stearate , PEG-100 stearte , cetyl alcohol , cetearyl alcohol, polysorbate 60 , propylene glycol, stearic acid , hydrogenated polyisobutene, dimethicone, triethanolamine , salicylic acid, imidazolidinyl urea, chondrus crispus (carrageenan) , methylparaben, propylparaben,mentha piperita (peppermint oil), chloroxylenol, dmdm hydantoin